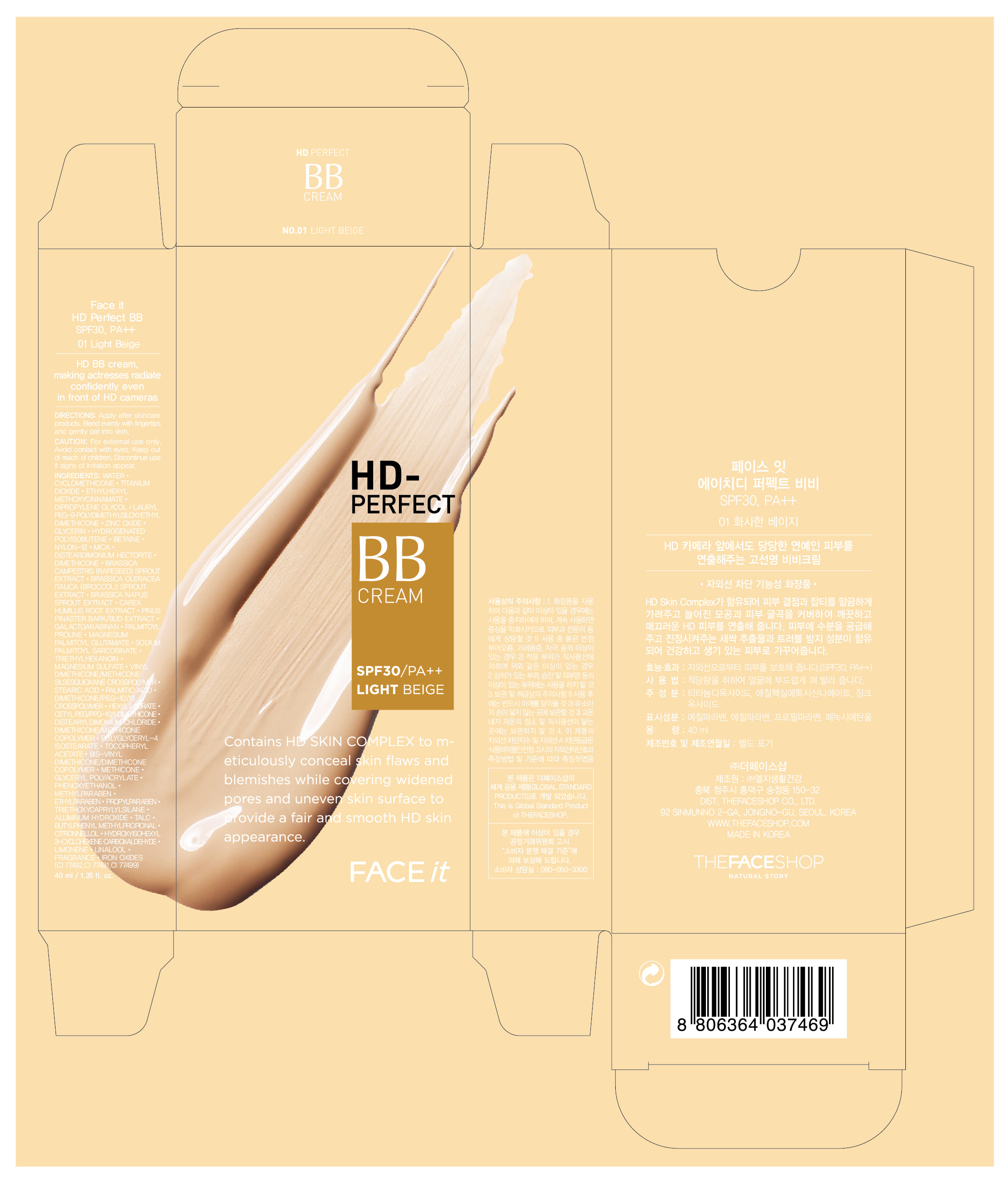 DRUG LABEL: FACE IT HD PERFECT BB SPF30 PA 01
NDC: 51523-103 | Form: CREAM
Manufacturer: THEFACESHOP CO., LTD
Category: otc | Type: HUMAN OTC DRUG LABEL
Date: 20110823

ACTIVE INGREDIENTS: OCTINOXATE 6 mL/100 mL; TITANIUM DIOXIDE 6.36 mL/100 mL; ZINC OXIDE 2.88 mL/100 mL; BETAINE 2 mL/100 mL; TALC 0.684 mL/100 mL
INACTIVE INGREDIENTS: WATER; CYCLOMETHICONE; DIPROPYLENE GLYCOL; DIMETHICONE; GLYCERIN; MICA; TITANIUM DIOXIDE; ALUMINUM HYDROXIDE; STEARIC ACID; DIMETHICONE; MAGNESIUM SULFATE, UNSPECIFIED; TRIETHOXYCAPRYLYLSILANE; POLYGLYCERYL-4 ISOSTEARATE; HEXYL LAURATE; PHENOXYETHANOL; TRIETHOXYCAPRYLYLSILANE; METHYLPARABEN; DISTEARYLDIMONIUM CHLORIDE; STEARIC ACID; CAREX HUMILIS ROOT; ETHYLPARABEN; PROPYLPARABEN; MICA; TRIETHYLHEXANOIN; MARITIME PINE

Drug Facts

ACTIVE INGREDIENT

OCTINOXATE (6%)
TITANIUM DIOXIDE (6.36%)
ZINC OXIDE (2.88%)
BETAINE (2%)
TALC (0.684%)

INACTIVE INGREDIENT

WATER, CYCLOMETHICONE, DIPROPYLENE GLYCOL, DIMETHICONE, GLYCERIN, MICA, TITANIUM DIOXIDE, ALUMINUM HYDROXIDE, STEARIC ACID, DIMETHICONE, MAGNESIUM SULFATE, TRIETHOXYCAPRYLYLSILANE, POLYGLYCERYL-4 ISOSTEARATE, HEXYL LAURATE, PHENOXYETHANOL, TRIETHOXYCAPRYLYLSILANE, METHYLPARABEN, DISTEARYLDIMONIUM CHLORIDE, STEARIC ACID, CAREX HUMILIS ROOT, ETHYLPARABEN, PROPYLPARABEN, MICA, TRIETHYLHEXANOIN, MARITIME PINE

PURPOSE

Provides high protection against sunburn and tanning.

WHEN USING

Avoid contact with eyes.

STOP USE

Discontinue use if sign of irritation or rash appear.

DOSAGE AND ADMINISTRATION

Dispense an adequate amount and apply evenly. (At the final stage of basic skincare, dispense an adequate amount and apply evenly to desired parts)

PACKAGE LABEL

FACE IT HD PERFECT BB SPF30 PA++ 01